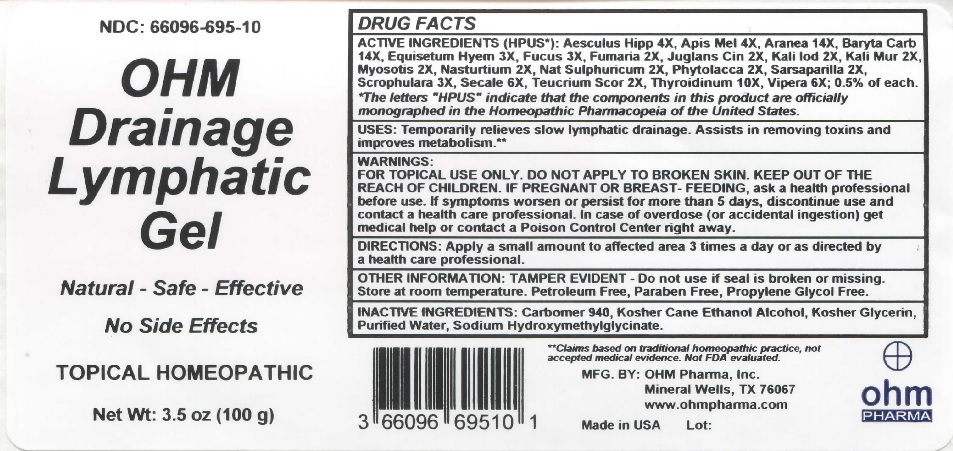 DRUG LABEL: OHM Drainage Lymphatic
NDC: 66096-695 | Form: GEL
Manufacturer: OHM PHARMA INC.
Category: homeopathic | Type: HUMAN OTC DRUG LABEL
Date: 20211229

ACTIVE INGREDIENTS: HORSE CHESTNUT 4 [hp_X]/100 g; APIS MELLIFERA 4 [hp_X]/100 g; ARANEUS DIADEMATUS 14 [hp_X]/100 g; BARIUM CARBONATE 14 [hp_X]/100 g; EQUISETUM HYEMALE 3 [hp_X]/100 g; FUCUS VESICULOSUS 3 [hp_X]/100 g; FUMARIA OFFICINALIS FLOWERING TOP 2 [hp_X]/100 g; JUGLANS CINEREA BRANCH BARK/ROOT BARK 2 [hp_X]/100 g; POTASSIUM IODIDE 2 [hp_X]/100 g; POTASSIUM CHLORIDE 2 [hp_X]/100 g; MYOSOTIS ARVENSIS 2 [hp_X]/100 g; NASTURTIUM OFFICINALE 2 [hp_X]/100 g; SODIUM SULFATE 2 [hp_X]/100 g; PHYTOLACCA AMERICANA ROOT 2 [hp_X]/100 g; SMILAX ORNATA ROOT 2 [hp_X]/100 g; SCROPHULARIA NODOSA 3 [hp_X]/100 g; CLAVICEPS PURPUREA SCLEROTIUM 6 [hp_X]/100 g; TEUCRIUM SCORODONIA FLOWERING TOP 2 [hp_X]/100 g; THYROID, UNSPECIFIED 10 [hp_X]/100 g; VIPERA BERUS VENOM 6 [hp_X]/100 g
INACTIVE INGREDIENTS: CARBOMER 940; ALCOHOL; GLYCERIN; WATER; SODIUM HYDROXYMETHYLGLYCINATE

OHM Drainage Lymphatic Gel

ACTIVE INGREDIENT

ACTIVE INGREDIENTS (HPUS*): Aesculus Hipp 4X, Apis Mel 4X, Aranea 14X, Baryta Carb 14X, Equisetum Hyem 3X, Fucus3X, Fumaria 2X, Juglans Cin 2X, Kali Iod 2X, Kali Mur 2X, Myosotis 2X, Nasturtium 2X, Nat Sulphuricum 2X, Phytolacca 2X, Sarsaparilla 2X, Scrophulara 3X, Secale 6X, Teucrium Scor 2X, Thyroidinum 10X, Vipera 6X; 0.5% of each.

*The letters "HPUS" indicate that the components in this product are officially monographed in the Homeopathic Pharmacopeia of the United States.

INDICATIONS AND USAGE

USES: Temporarily relieves slow lymphatic drainage. Assists in removing toxins and improves metabolism.**

**Claims based on traditional homeopathic practice, not accepted medical evidence. Not FDA evaluated.

WARNINGS

WARNINGS: FOR TOPICAL USE ONLY. DO NOT APPLY TO BROKEN SKIN. IF PREGNANT OR BREAST-FEEDING, ask a health professional before use. If symptoms worsen or persist for more than 5 days, discontinue use and contact a health care professional. In case of overdose (or accidental ingestion) get medical help or contact a Poison Control Center right away.

- KEEP OUT OF REACH OF CHILDREN.

DOSAGE AND ADMINISTRATION

DIRECTIONS: Apply a small amount to affected area 3 times a day or as directed by a health care professional.

OTHER INFORMATION: TAMPER EVIDENT - Do not use if seal is broken or missing. Store at room temperature. Petroleum Free, Paraben Free, Propylene Glycol Free.

INACTIVE INGREDIENT

INACTIVE INGREDIENTS: Carbomer 940, Kosher Cane Ethanol Alcohol, Kosher Glycerin, Organic Aloe Vera, Purified Water, Sodium Hydroxymethylglycinate.

QUESTIONS

MFG. BY: OHM Pharma, Inc. Mineral Wells, TX 76067

www.ohmpharma.com

PACKAGE LABEL

NDC: 66096-695-10

OHM Drainage Lymphatic Gel

Natural - Safe - Effective

No Side Effects

TOPICAL homeopathic

Net Wt: 3.5 oz (100 g)

Made in USA

PURPOSE

Relieves slow lymphatic drainage, assists in removing toxins and improves metabolism.